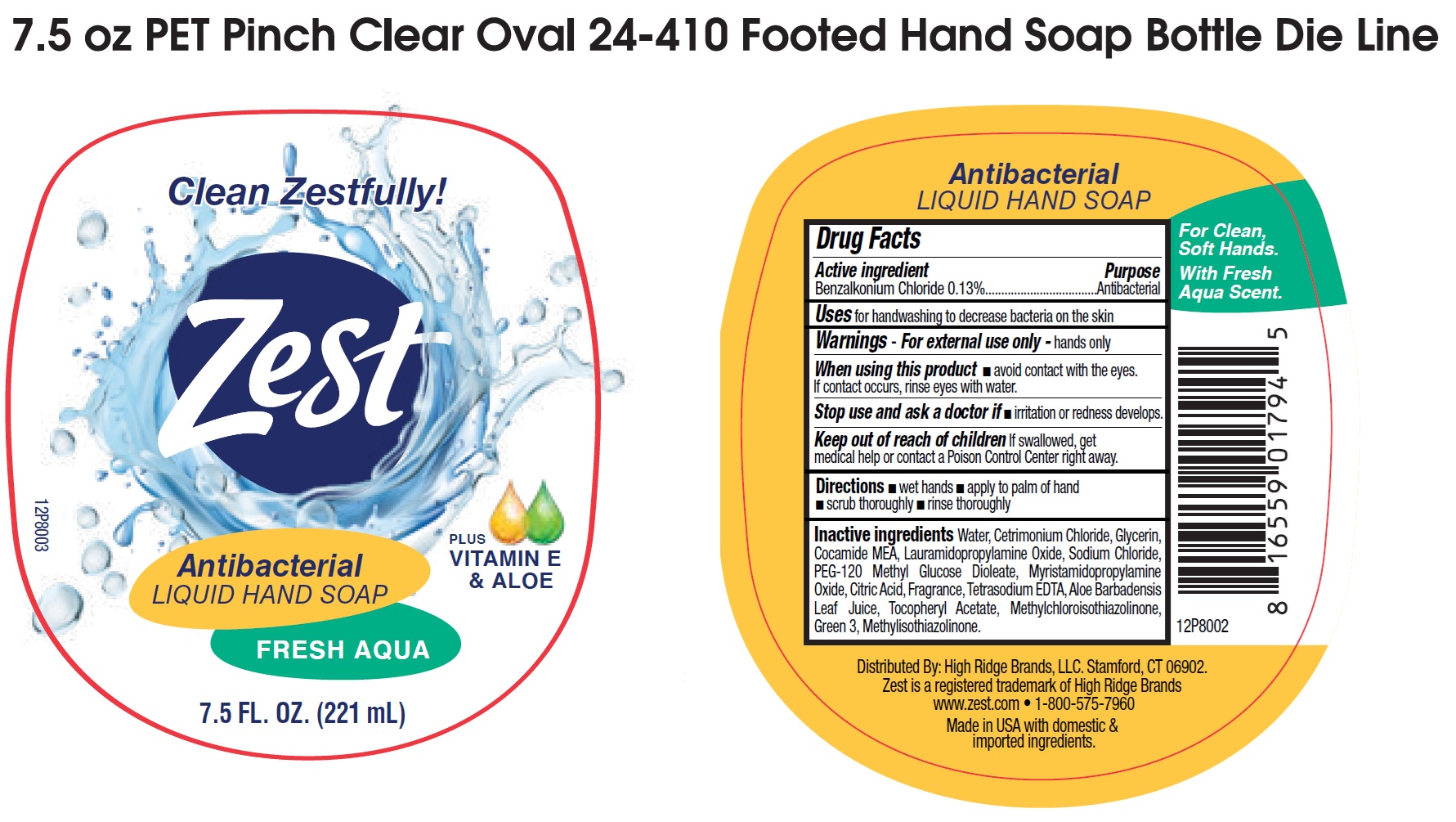 DRUG LABEL: Zest Antibacterial Liquid Hand Soap, Fresh Aqua
NDC: 81277-013 | Form: GEL
Manufacturer: Sodalis USA, LLC
Category: otc | Type: HUMAN OTC DRUG LABEL
Date: 20250218

ACTIVE INGREDIENTS: BENZALKONIUM CHLORIDE 1.3 mg/1 mL
INACTIVE INGREDIENTS: WATER; CETRIMONIUM CHLORIDE; GLYCERIN; COCAMIDE MEA; LAURAMIDOPROPYLAMINE OXIDE; SODIUM CHLORIDE; PEG-120 METHYL GLUCOSE DIOLEATE; MYRISTAMIDOPROPYLAMINE OXIDE; CITRIC ACID MONOHYDRATE; EDETATE SODIUM; ALOE VERA LEAF; .ALPHA.-TOCOPHEROL ACETATE; METHYLCHLOROISOTHIAZOLINONE; FD&C GREEN NO. 3; METHYLISOTHIAZOLINONE

Zest Antibacterial Liquid Hand Soap, Fresh Aqua

Active ingredient

Benzalkonium Chloride 0.13%

Purpose

Antibacterial

Uses

for handwashing to decrease bacteria on the skin

Warnings

For external use only- hands only

When using this product

• avoid contact with the eyes. If contact occurs, rinse eyes with water.

Stop use and ask a doctor if

• irritation or redness develops.

Keep out of reach of children

If swallowed, get medical help or contact a Poison Control Center right away.

Directions

• wet hands

• apply to palm of hand

• scrub thoroughly

• rinse thoroughly

Inactive ingredients:

Water, Cetrimonium Chloride, Glycerin, Cocamide MEA, Lauramidopropylamine Oxide, Sodium Chloride, PEG-120 Methyl Glucose Dioleate, Myristamidopropylamine Oxide, Citric Acid, Fragrance, Tetrasodium EDTA, Aloe Barbadensis Leaf Juice, Tocopheryl Acetate, Methylchloroisothiazolinone, Green 3, Methylisothiazolinone.